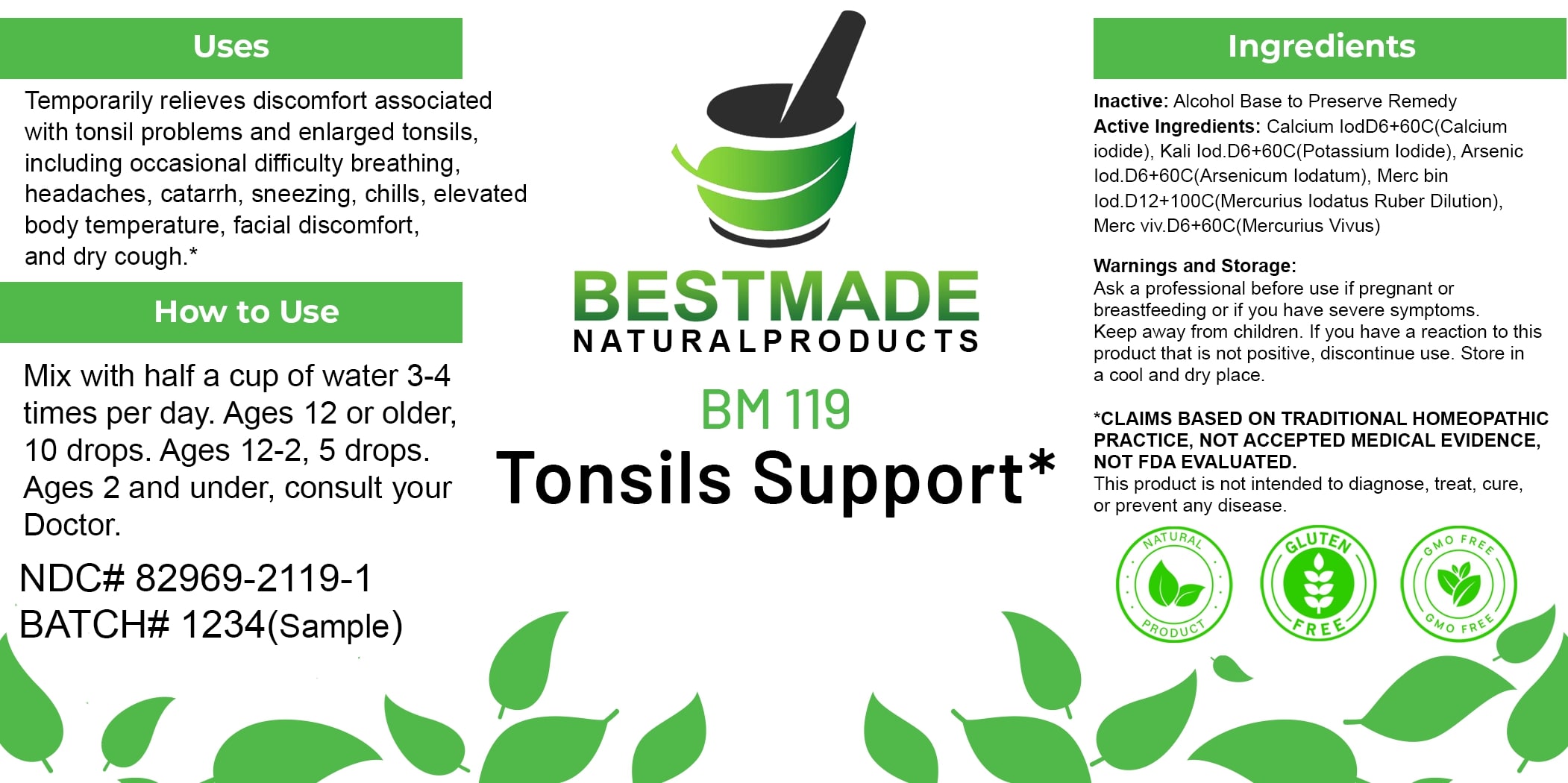 DRUG LABEL: Bestmade Natural Products BM119
NDC: 82969-2119 | Form: LIQUID
Manufacturer: Bestmade Natural Products
Category: homeopathic | Type: HUMAN OTC DRUG LABEL
Date: 20250207

ACTIVE INGREDIENTS: CALCIUM IODIDE 60 [hp_C]/60 [hp_C]; MERCURIC IODIDE 60 [hp_C]/60 [hp_C]; MERCURY 60 [hp_C]/60 [hp_C]; POTASSIUM IODIDE 60 [hp_C]/60 [hp_C]; ARSENIC TRIIODIDE 60 [hp_C]/60 [hp_C]
INACTIVE INGREDIENTS: ALCOHOL 60 [hp_C]/60 [hp_C]

BM119

DOSAGE AND ADMINISTRATION

How to Use

Mix with half a cup of water 3-4 times per day. Ages 12 or older, 10 drops. Ages 12-2, 5 drops. Ages 2 and under, consult your Doctor.

INACTIVE INGREDIENT

Ingredients

Inactive: Alcohol Base to Preserve Remedy

ACTIVE INGREDIENT

Active Ingredients: Calcium IodD6+60Cr(Calcium Iodide), Kali Iod D6+60C(Potassium Iodide), Arsenic Iod D6+60C(Arsenicum Iodatum), Merc bin Iod D12+100C(Mercurius Iodatus Ruber Dillon), Merc viv D6+60C(Mercurius Vivus)

Uses

Temporarily relieves discomfort associated with tonsil problems and enlarged tonsils, including occasional difficulty breathing, headaches, catarrh, sneezing, chills, elevated body temperature, facial discomfort, and dry cough.*

*CLAIMS BASED ON TRADITIONAL HOMEOPATHIC PRACTICE, NOT ACCEPTED MEDICAL EVIDENCE. NOT FDA EVALUATED.

This product is not intended to diagnose, treat, cure, or prevent any disease.

Uses

Temporarily relieves discomfort associated with tonsil problems and enlarged tonsils, including occasional difficulty breathing, headaches, catarrh, sneezing, chills, elevated body temperature, facial discomfort, and dry cough.*

*CLAIMS BASED ON TRADITIONAL HOMEOPATHIC PRACTICE, NOT ACCEPTED MEDICAL EVIDENCE. NOT FDA EVALUATED.

This product is not intended to diagnose, treat, cure, or prevent any disease.

KEEP OUT OF REACH OF CHILDREN

Warnings and Storage:

Ask a professional before use if pregnant or breastfeeding or if you have severe symptoms. Keep away from children. If you have a reaction to this product that is not positive, discontinue use. Store in a cool and dry place.

Warnings and Storage:

Ask a professional before use if pregnant or breastfeeding or if you have severe symptoms. Keep away from children. If you have a reaction to this product that is not positive, discontinue use. Store in a cool and dry place.

*CLAIMS BASED ON TRADITIONAL HOMEOPATHIC PRACTICE, NOT ACCEPTED MEDICAL EVIDENCE. NOT FDA EVALUATED. This product is not intended to diagnose, treat, cure, or prevent any disease.

Entire package label